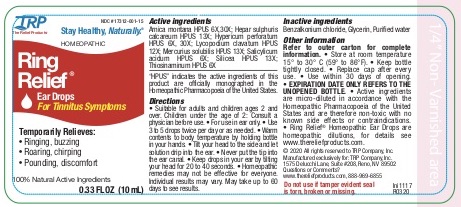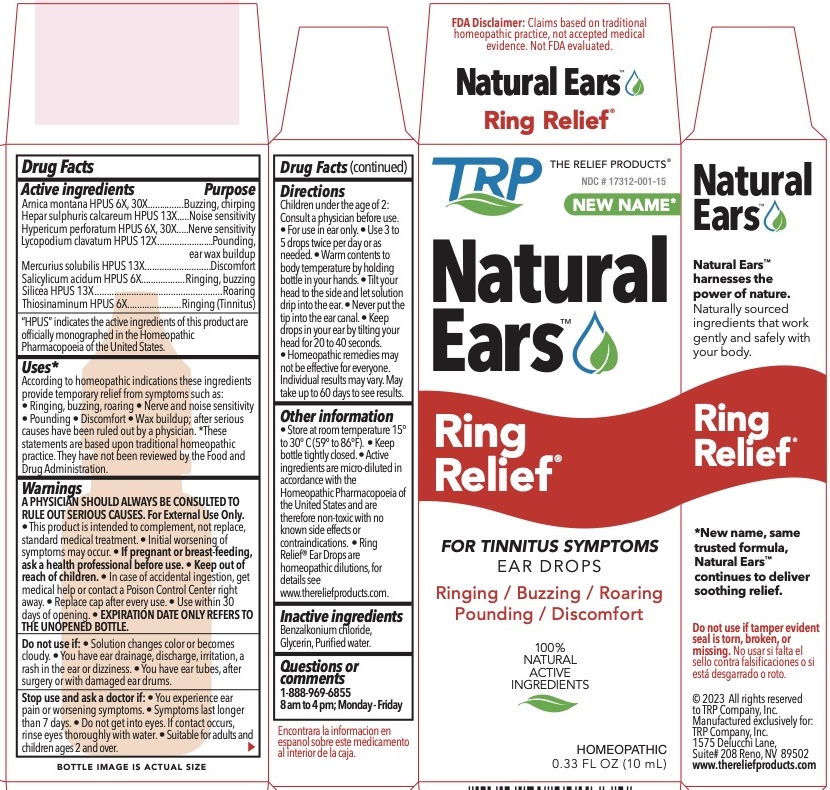 DRUG LABEL: Ring Relief
NDC: 17312-001 | Form: LIQUID
Manufacturer: TRP Company
Category: homeopathic | Type: HUMAN OTC DRUG LABEL
Date: 20251215

ACTIVE INGREDIENTS: ARNICA MONTANA 6 [hp_X]/1 mL; CALCIUM SULFIDE 13 [hp_X]/1 mL; HYPERICUM PERFORATUM 6 [hp_X]/1 mL; LYCOPODIUM CLAVATUM SPORE 12 [hp_X]/1 mL; MERCURIUS SOLUBILIS 13 [hp_X]/1 mL; SALICYLIC ACID 6 [hp_X]/1 mL; SILICON DIOXIDE 13 [hp_X]/1 mL; ALLYLTHIOUREA 6 [hp_X]/1 mL
INACTIVE INGREDIENTS: BENZALKONIUM CHLORIDE; GLYCERIN; WATER

Ring Relief

ACTIVE INGREDIENT

Arnica montana HPUS 6x, 30x
Hepar sulph calc HPUS 13x
Hypericum perforatum HPUS 6x, 30x
Lycopodium clavatum HPUS 12x
Mercurius sol HPUS 13x
Salicylicum acidum HPUS 6x
Silicea HPUS 13x
Thiosinaminum HPUS 6x

"HPUS" indicates the active ingredients are in the Homeopathic Pharmacopoeia of the United States.

PURPOSE

Arnica montana HPUS - Buzzing, Chirping
Hepar sulph calc HPUS - Noise sensitivity
Hypericum perforatum HPUS - Nerve sensitivity
Lycopodium clavatum HPUS - Pounding, wax buildup
Mercurius sol HPUS - Discomfort
Salicylicum acidum HPUS - Ringing, Buzzing
Silicea HPUS - Roaring
Thiosinaminum HPUS - Ringing (Tinnitus)

Uses:*
According to homeopathic indications, these ingredients temporarily relieve Tinnitus symptoms such as: • Ringing • Buzzing • Roaring • Nerve and Noise Sensitivity • Pounding • Discomfort • Wax buildup after serious causes have been ruled out by a physician.
*These statements are based upon traditional homeopathic practice. They have not been reviewed by the Food and Drug Administration.

Warnings:

A PHYSICIAN SHOULD ALWAYS BE CONSULTED TO RULE OUT SERIOUS CAUSES. For External Use Only.

- This product is intended to complement, not replace, standard medical treatment.
- Initial worsening of symptoms may occur.

PREGNANCY OR BREAST FEEDING

If pregnant or breast-feeding, ask a health professional before use.

Do not use:

- If solution changes color or becomes cloudy.
- If you have ear drainage, discharge, irritation, a rash in the ear or dizziness.
- If you have ear tubes, after surgery or with damaged ear drums.

WARNINGS

- In case of accidental ingestion, get medical help or contact a Poison Control Center right away.
- Do not get into eyes. If contact occurs, rinse eyes thoroughly with water.

Directions:
Suitable for adults and children ages 2 and over.

• Children under the age of 2: consult a physician before use.

• For use in ear only.

• Use 3 to 5 drops twice per day or as needed.
• Warm contents to body temperature by holding in your hands. Tilt your head to the side and let solution drip into the ear. Never put the tip into the ear canal.
• Keep drops in your ear by tilting your head for 20-40 seconds.
Homeopathic remedies may not be effective for everyone.
May take up to 60 days to see results.

Other information:
There are no known contraindications. Active ingredients are micro-diluted in accordance with the Homeopathic Pharmacopoeia of the United States and are therefore non-toxic with no known side effects. Store in a cool dark location. Ring Relief® Ear Drops are homeopathic dilutions, for details see www.thereliefproducts.com.

Inactive Ingredients:
Benzalkonium Chloride, Glycerin, Purified Water.

Questions or comments?

www.thereliefproducts.com, 1-888-969-6855

Stop Use

Stop use and ask a doctor if: • You experience ear pain or worsening symptoms. • Your symptoms last longer than 7 days.